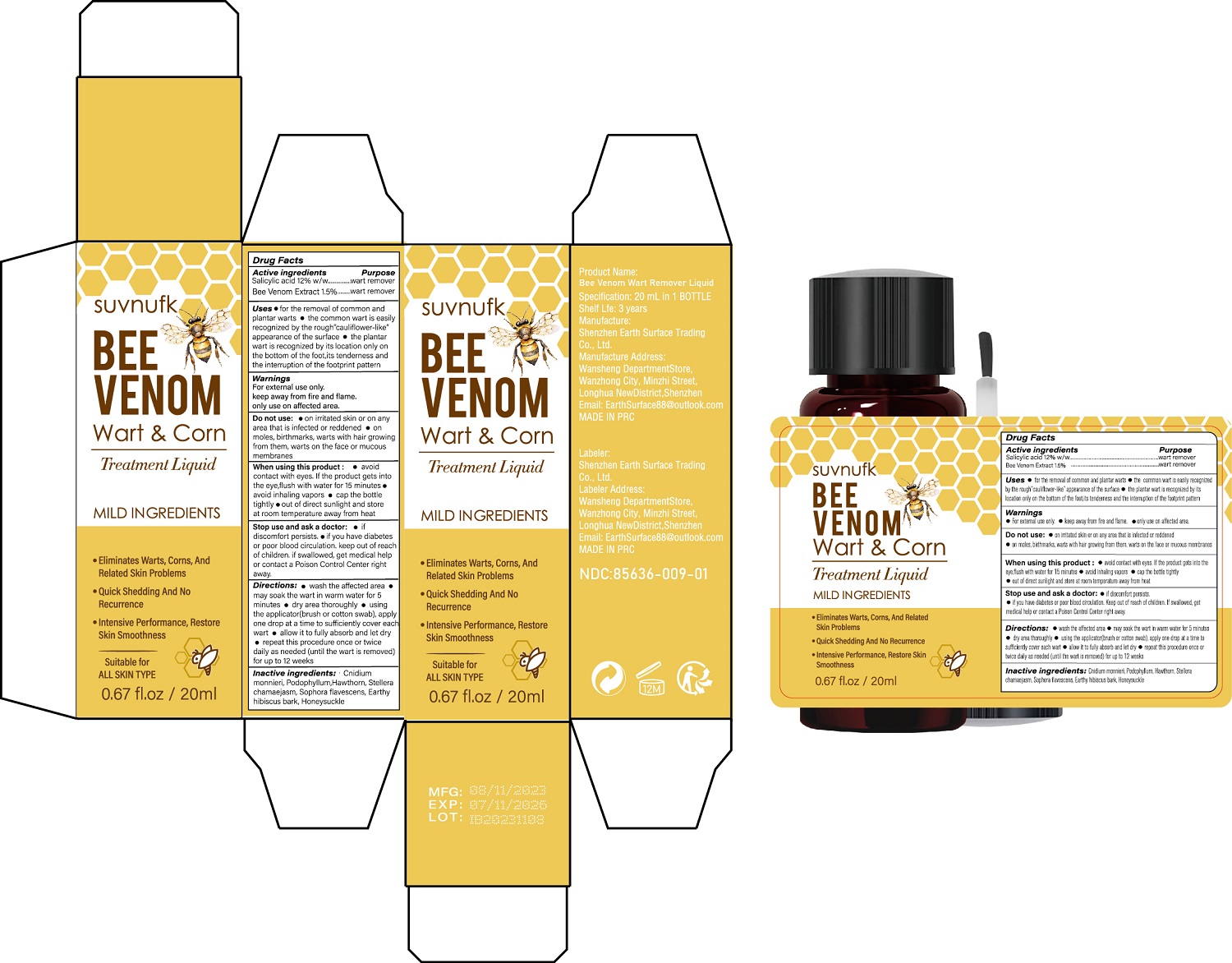 DRUG LABEL: Bee Venom Wart Remover Liquid
NDC: 85636-009 | Form: LIQUID
Manufacturer: Shenzhen Earth Surface Trading Co., Ltd.
Category: otc | Type: HUMAN OTC DRUG LABEL
Date: 20250910

ACTIVE INGREDIENTS: SALICYLIC ACID 12 g/100 mL
INACTIVE INGREDIENTS: CNIDIUM MONNIERI FRUIT; HAWTHORN LEAF WITH FLOWER; LONICERA JAPONICA FLOWER; STELLERA CHAMAEJASME WHOLE; HIBISCUS SYRIACUS BARK; SOPHORA FLAVESCENS ROOT; PODOPHYLLUM; APIS MELLIFERA VENOM

ACTIVE INGREDIENT

Salicylic acid 12%

Bee Venom Extract 1.5%

Purpose

wart remover

Uses

Uses · for the removal of common and
plantar warts · the common wart is easily
recognized by the rough”cauliflower-like”
appearance of the surface · the plantar
wart is recognized by its location only on
the bottom of the foot,its tenderness and
the interruption of the footprint pattern

Warnings

For external use only.
keep away from fire and flame.
only use on affected area.

When using this product :

· avoid contact with eyes. If the product gets into the eye,flush with water for 15 minutes

· avoid inhaling vapors

· cap the bottle tightly

·out of direct sunlight and store at room temperature away from heat

Keep Out Of Reach Of Children

Directions Of Safe Use:

● wash the affected area ● may soak the tag in warm
water for 5 minutes ● dry area thoroughly ● using the
applicator(brush swab), apply one drop at a time to
sufficiently cover each tag ● allow it to fully absorb a
nd let dry ● repeat this procedure once or twice daily
as needed (until the tag falling off) for up to 12 weeks

Stop use and ask a doctor:

· if discomfort persists.·if you have diabetes
or poor blood circulation.Keep out of reach
of children. lf swallowed, get medical help
or contact a Poison Control Center right
away.

Inactive ingredients

Cnidium monnieri, Podophyllum,Hawthorn, Stellera chamaejasm, Sophora flavescens, Earthy hibiscus bark, Honeysuckle